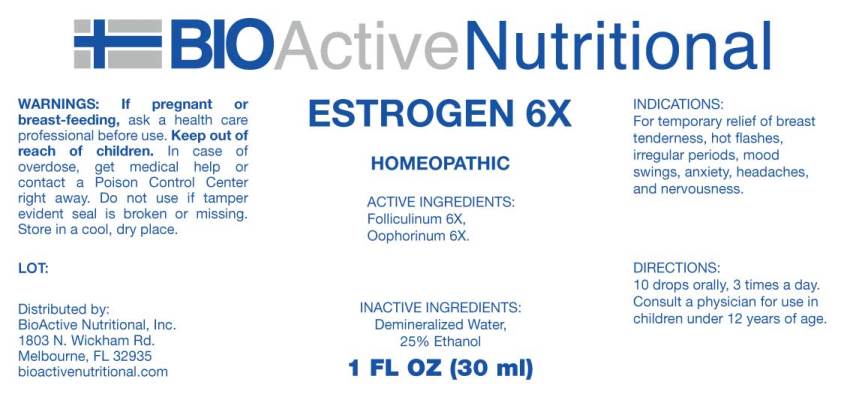 DRUG LABEL: Estrogen
NDC: 43857-0074 | Form: LIQUID
Manufacturer: BioActive Nutritional, Inc.
Category: homeopathic | Type: HUMAN OTC DRUG LABEL
Date: 20180822

ACTIVE INGREDIENTS: ESTRONE 6 [hp_X]/1 mL; SUS SCROFA OVARY 6 [hp_X]/1 mL
INACTIVE INGREDIENTS: WATER; ALCOHOL

Drug Facts:

ACTIVE INGREDIENTS:

Folliculinum 6X, Oophorinum (Suis) 6X.

INDICATIONS:

For temporary relief of breast tenderness, hot flashes, irregular periods, mood swings, anxiety, headaches, and nervousness.

WARNINGS:

If pregnant or breast-feeding, ask a health professional before use.

Keep out of reach of children. In case of overdose, get medical help or contact a Poison Control Center right away.

Do not use if tamper evident seal is broken or missing.

Store in cool, dry place.

DIRECTIONS:

10 drops orally, 3 times a day. Consult a physician for use in children under 12 years of age.

INACTIVE INGREDIENTS:

Demineralized water, 25% Ethanol.

Keep out of reach of children. In case of overdose, get medical help or contact a Poison Control Center right away.

INDICATIONS:

For temporary relief of breast tenderness, hot flashes, irregular periods, mood swings, anxiety, headaches, and nervousness.

QUESTIONS:

Distributed by:
BioActive Nutritional, Inc.
1803 N. Wickham Rd.
Melbourne, FL 32935
bioactivenutritional.com

PACKAGE DISPLAY LABEL:

BIOActive Nutritional

ESTROGEN 6X

HOMEOPATHIC

1 FL OZ (30 ml)